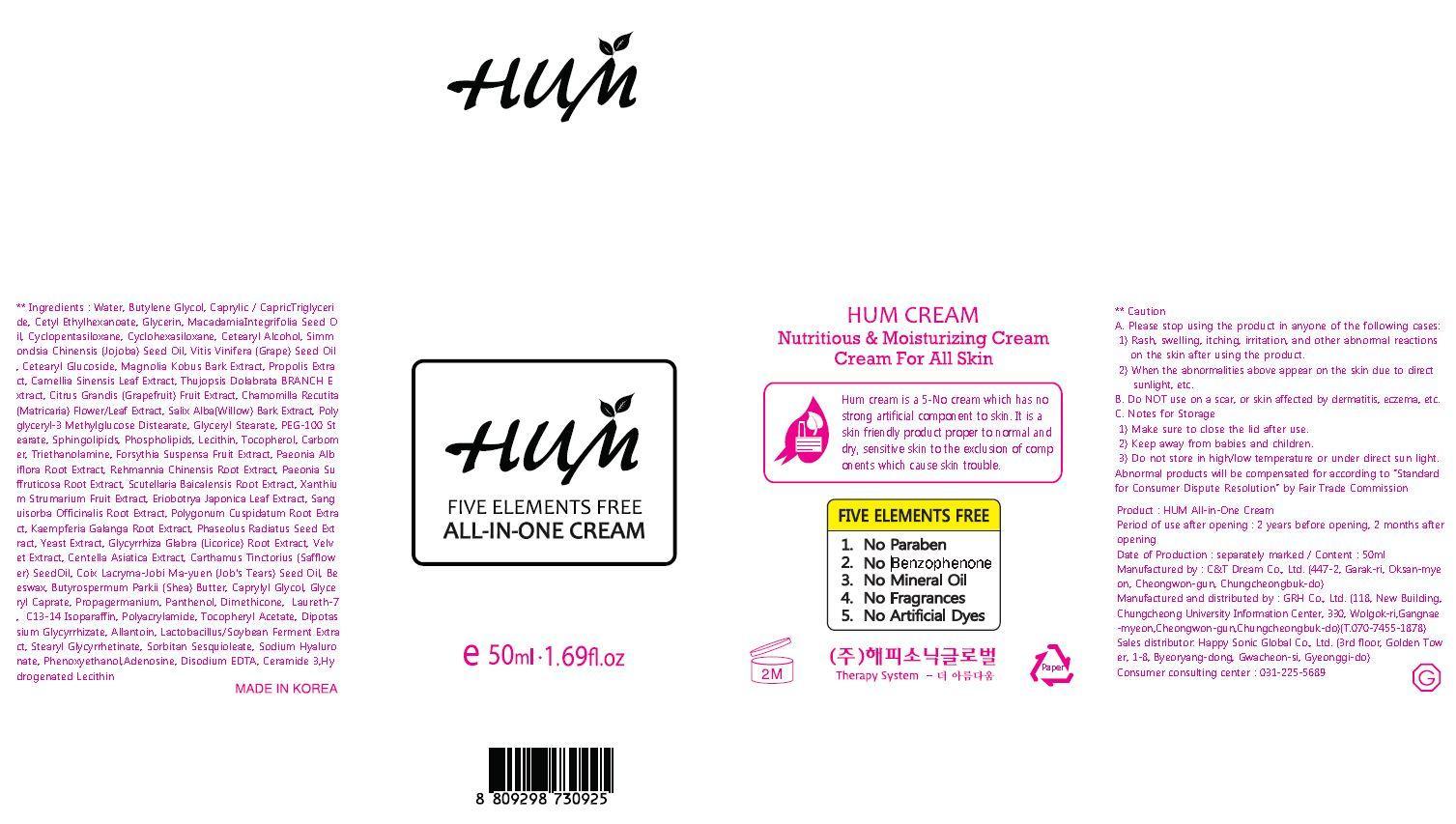 DRUG LABEL: HUM
NDC: 61254-1001 | Form: CREAM
Manufacturer: Happy Sonic Global Co., Ltd.
Category: otc | Type: HUMAN OTC DRUG LABEL
Date: 20131210

ACTIVE INGREDIENTS: GLYCERIN 0.1 g/100 mL
INACTIVE INGREDIENTS: BUTYLENE GLYCOL; ALCOHOL; CAMELLIA SINENSIS ROOT; TOCOPHEROL

Drug Facts

ACTIVE INGREDIENT

glycerin

INACTIVE INGREDIENT

Water, Butylene Glycol, Caprylic / CapricTriglyceride, Cetyl Ethylhexanoate, Glycerin, MacadamiaIntegrifolia Seed Oil, Cyclopentasiloxane, Cyclohexasiloxane, Cetearyl Alcohol, Simmondsia Chinensis (Jojoba) Seed Oil, Vitis Vinifera (Grape) Seed Oil, Cetearyl Glucoside, Magnolia Kobus Bark Extract, Propolis Extract, Camellia Sinensis Leaf Extract, Thujopsis Dolabrata BRANCH Extract, Citrus Grandis (Grapefruit) Fruit Extract, Chamomilla Recutita (Matricaria) Flower/Leaf Extract, Salix Alba(Willow) Bark Extract, Poly glyceryl-3 Methylglucose Distearate, Glyceryl Stearate, PEG-100 Stearate, Sphingolipids, Phospholipids, Lecithin, Tocopherol, Carbomer, Triethanolamine, Forsythia Suspensa Fruit Extract, Paeonia Albiflora Root Extract, Rehmannia Chinensis Root Extract, Paeonia Suffruticosa Root Extract, Scutellaria Baicalensis Root Extract, Xanthium Strumarium Fruit Extract, Eriobotrya Japonica Leaf Extract, Sanguisorba Officinalis Root Extract, Polygonum Cuspidatum Root Extract, Kaempferia Galanga Root Extract, Phaseolus Radiatus Seed Extract, Yeast Extract, Glycyrrhiza Glabra (Licorice) Root Extract, Velvet Extract, Centella Asiatica Extract, Carthamus Tinctorius (Safflower) SeedOil, Coix Lacryma-Jobi Ma-yuen (Job's Tears) Seed Oil, Beeswax, Butyrospermum Parkii (Shea) Butter, Caprylyl Glycol, Glyceryl Caprate, Propagermanium, Panthenol, Dimethicone, Laureth-7, C13-14 Isoparaffin, Polyacrylamide, Tocopheryl Acetate, Dipotassium Glycyrrhizate, Allantoin, Lactobacillus/Soybean Ferment Extract, Stearyl Glycyrrhetinate, Sorbitan Sesquioleate, Sodium Hyaluronate, Phenoxyethanol,Adenosine, Disodium EDTA, Ceramide 3,Hydrogenated Lecithin

PURPOSE

skin protectant

keep out of reach of the children

INDICATIONS AND USAGE

apply a certain quantity to the skin every morning and night

WARNINGS

A. Please stop using the product in anyone of the following cases:
1) Rash, swelling, itching, irritation, and other abnormal reactions on the skin after using the product.
2) When the abnormalities above appear on the skin due to direct sunlight, etc.
B. Do NOT use on a scar, or skin affected by dermatitis, eczema, etc.
C. Notes for Storage
1) Make sure to close the lid after use.
2) Keep away from babies and children.
3) Do not store in high/low temperature or under direct sun light.
Abnormal products will be compensated for according to “Standard for Consumer Dispute Resolution” by Fair Trade Commission

DOSAGE AND ADMINISTRATION

for topical use only